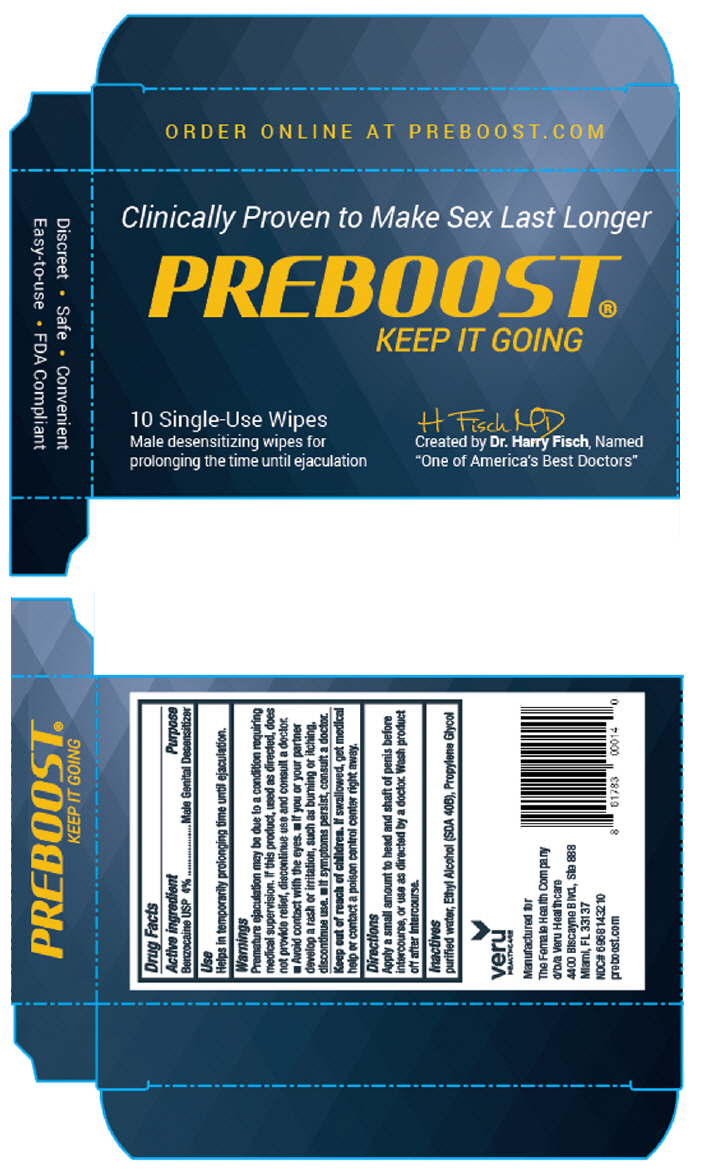 DRUG LABEL: Preboost
NDC: 69681-432 | Form: LIQUID
Manufacturer: The Female Health Company d/b/a Veru Healthcare
Category: otc | Type: HUMAN OTC DRUG LABEL
Date: 20170407

ACTIVE INGREDIENTS: benzocaine 4 g/100 mL
INACTIVE INGREDIENTS: alcohol; water; propylene glycol

PREBOOST®

Drug Facts

Active Ingredient

Benzocaine USP 4%

Purpose

Male Genital Desensitizer

Use

Helps in temporarily prolonging time until ejaculation

Warnings

STOP USE

Premature ejaculation may be due to a condition requiring medical supervision. If this product, used as directed, does not provide relief, discontinue use and consult a doctor.

- Avoid contact with the eyes.
- If you or your partner develops a rash or irritation, such as burning or itching, discontinue use.
- If symptoms persist, consult a doctor.

Keep out of reach of children. If swallowed, get medical help or contact a poison control center right away.

Directions

Apply a small amount to head and shaft of penis before intercourse, or use as directed by a doctor. Wash product off after intercourse.

Inactives

Purified water, Ethyl Alcohol (SDA 40B), Propylene Glycol

PRINCIPAL DISPLAY PANEL - 10 Wipes Packet Box

Clinically Proven to Make Sex Last Longer

PREBOOST®
KEEP IT GOING

10 Single-Use Wipes
Male desensitizing wipes for
prolonging the time until ejaculation

H Fisch MD
Created by Dr. Harry Fisch, Named
"One of America's Best Doctors"